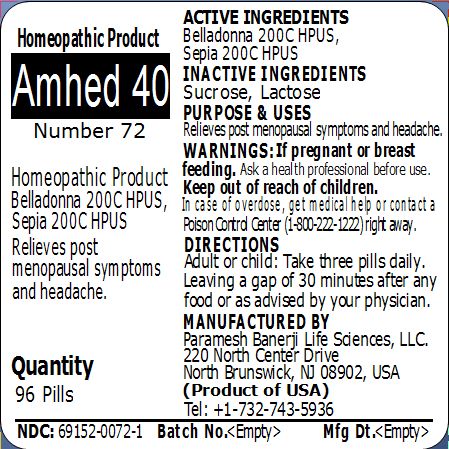 DRUG LABEL: Amhed 40 (Number 72)
NDC: 69152-0072 | Form: PELLET
Manufacturer: Paramesh Banerji Life Sciences LLC
Category: homeopathic | Type: HUMAN OTC DRUG LABEL
Date: 20150220

ACTIVE INGREDIENTS: ATROPA BELLADONNA 200 [hp_C]/1 1; SEPIA OFFICINALIS JUICE 200 [hp_C]/1 1
INACTIVE INGREDIENTS: SUCROSE; LACTOSE

Active Ingredients

Belladonna 200C HPUS, Sepia 200C HPUS

Inactive Ingredients

Sucrose, Lactose

Purpose

Relieves post menopausal symptoms and headache

Uses

Relieves post menopausal symptoms and headache

Warnings

If pregnant or breast feeding ask a health professional before use.

Keep out of reach of children. In case of overdose, get medical help or contact a Poison Control Center (1-800-222-1222) right away.

Direction

Adult or child: Take three pills daily. Leaving a gap of 30 minutes after any food or as advised by your physician.

Manufactured by

Paramesh Banerji Life Sciences, LLC

220 North Center Drive

North Brunswick, NJ 08902, USA

Product of USA

Tel: +1-732-743-5936

Principal Display Panel

Homeopathic Product

Amhed 40

Number 72

Homeopathic Product

Belladonna 200C HPUS, Sepia 200C HPUS

Relieves post menopausal symptoms and headache

Quantity

96 Pills